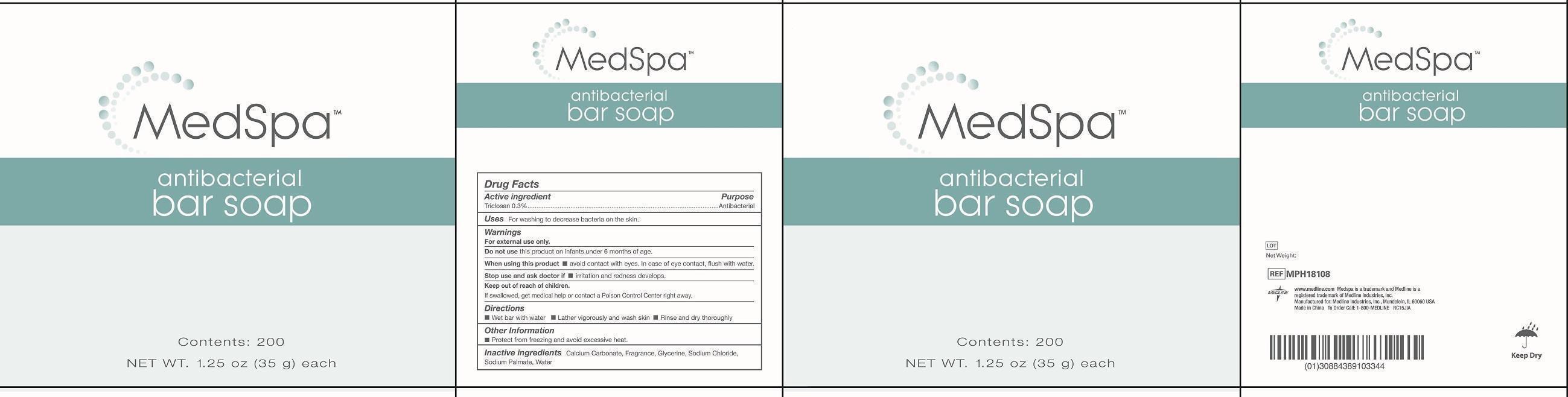 DRUG LABEL: medspa antibacterial bar
NDC: 69688-002 | Form: SOAP
Manufacturer: Jiangsu Xinheyuan Plastic Daily Chemical Co., Ltd.
Category: otc | Type: HUMAN OTC DRUG LABEL
Date: 20150609

ACTIVE INGREDIENTS: TRICLOSAN 0.3 g/100 g
INACTIVE INGREDIENTS: WATER; SODIUM PALMATE; CALCIUM CARBONATE; GLYCERIN; SODIUM CHLORIDE

Active Ingredient

Triclosan 0.3%

Purpose

Antibacterial

Uses

for washing to decrease bacteria on the skin.

Warnings

For external use only.

When using this product

Avoid contact with eyes. In case of eye contact, flush with water.

Don't use this product on infants under 6 months of age.

Stop use and ask a doctor

If irritation and redness develops.

Keep out of reach of children.

If swallowed, get medical help or contact a Poison Control Center right away.

Directions

- wet bar with water
- lather vigorously and wash skin
- rinse and dry thoroughly.

Inactive Ingredients

Water, calcium carbonate, fragrance, glycerine, sodium chloride, sodium palmate